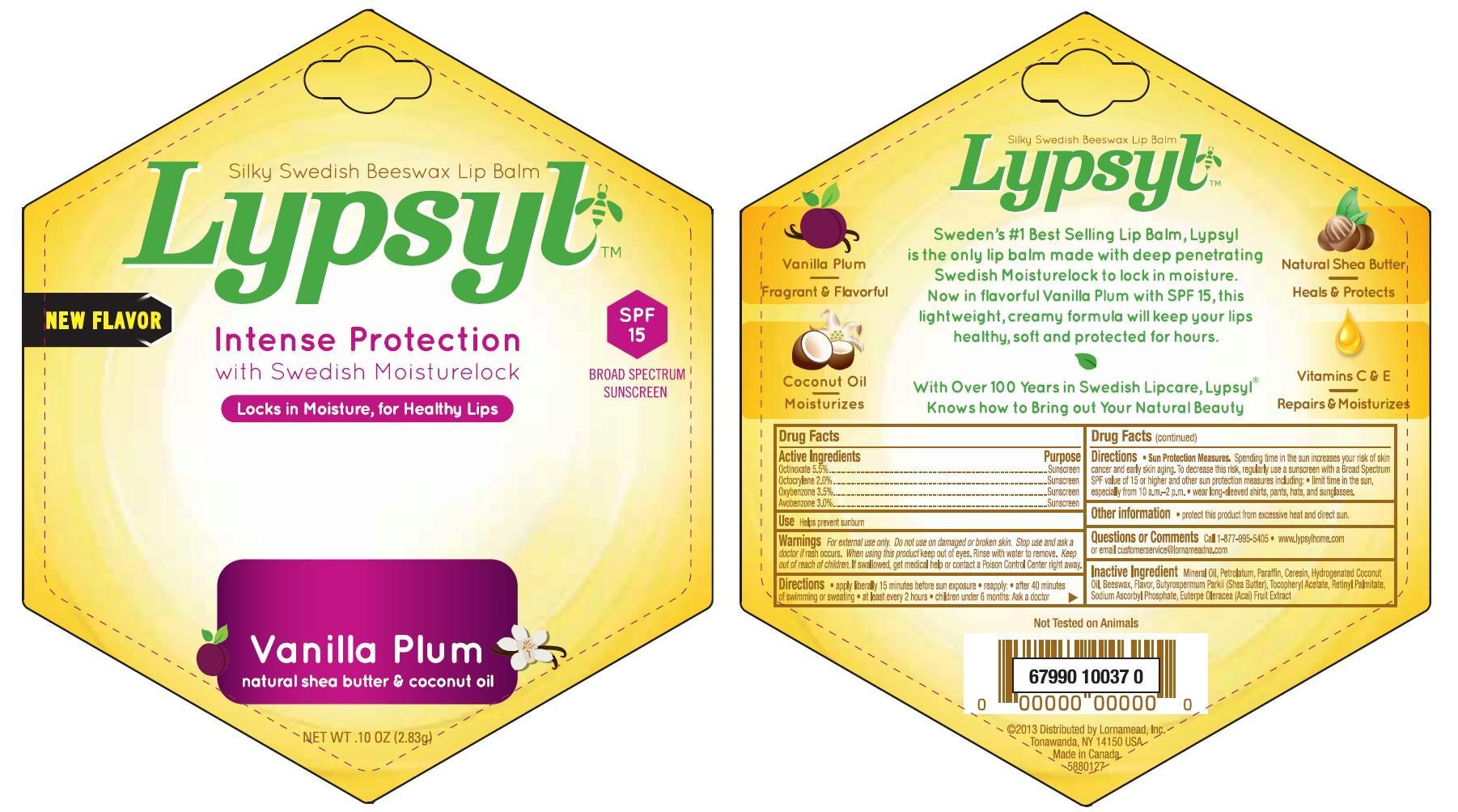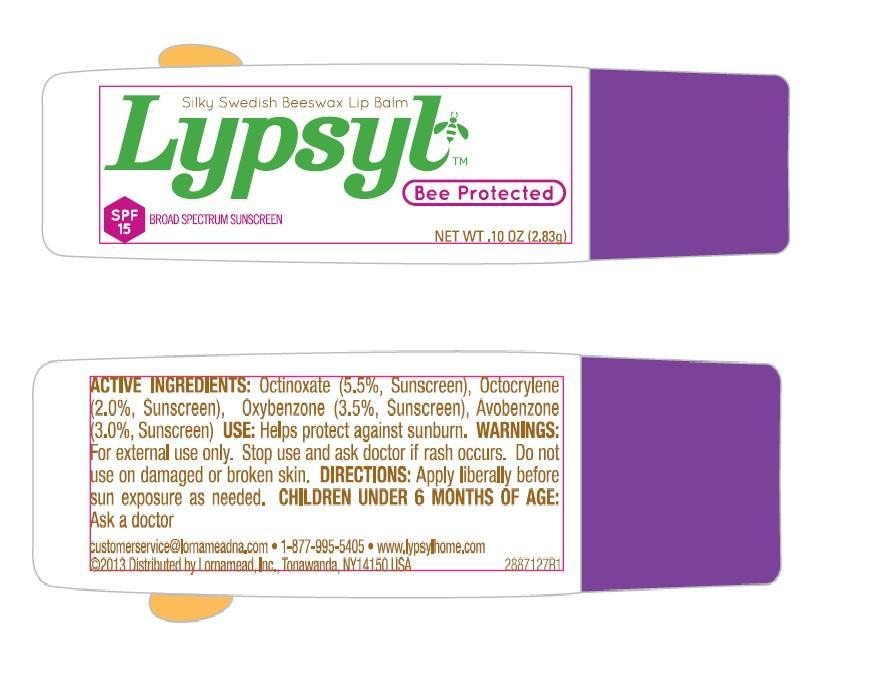 DRUG LABEL: LypSyl Vanilla Plum
NDC: 62721-8127 | Form: LIPSTICK
Manufacturer: Lornamead
Category: otc | Type: HUMAN OTC DRUG LABEL
Date: 20131213

ACTIVE INGREDIENTS: OCTINOXATE 5.5 g/100 g; OCTOCRYLENE 2.0 g/100 g; AVOBENZONE 3.0 g/100 g; OXYBENZONE 3.5 g/100 g
INACTIVE INGREDIENTS: VITAMIN A PALMITATE; ALPHA-TOCOPHEROL; YELLOW WAX; MINERAL OIL; PETROLATUM; SHEA BUTTER; CERESIN; PARAFFIN; SODIUM ASCORBYL PHOSPHATE; HYDROGENATED COCONUT OIL; ACAI

Active Ingredients

Octyl Methoxycinnamate 5.5%...................................Sunscreen

Octylcrylene 2.0%....................................................Sunscreen

Oxybenzone 3.5%....................................................Sunscreen

Avobenzone 3.0%.....................................................Sunscreen

Inactive Ingredients

Beeswax, Butyrospermum Parkii (Shea Butter), Ceresin, Euterpe Oleracea (Acai) Fruit Extract, Flavor, Hydrogenated Coconut Oil, Mineral Oil, Paraffin, Petrolatum, Retinyl Palmitate (Vitamin A Palmitate), Sodium Ascorbyl Phosphate, Tocopheryl Acetate

Directions

- apply liberally 15 minutes before sun exposure
- after 40 minutes of swimming or sweating
- at least every 2 hours
- children under 6 months: ask a doctor

Sun protection measures. Spending time in the sun increases your risk of skin cancer and early skin aging. To decrease this risk, regularly use a sunscreen with Broad Spectrum SPF vlaue of 15 or higher and other sun protection measures including

- limit time in the sun, especially from 10a.m. -2 p.m.
- wear long-sleeved shirts, pants hats and sunglasses

Other Information

Protect this product from excessive heat and direct sun.

Use

Helps prevent sunburn

Warnings

For external use only. Do not use on damaged or broken skin. Stop use and ask a doctor if rash occurs. When using this product keep out of eyes. Rinse with water to remove.

Keep out of reach of children

If swallowed, get medical help or contact a Poison Control Center right away

Questions or Comments

- call 877-995-5405
- www.lypsylhome.com
- or email customerservice @lornameadna.com

PACKAGE LABEL

MM1.jpg

MM2.jpg